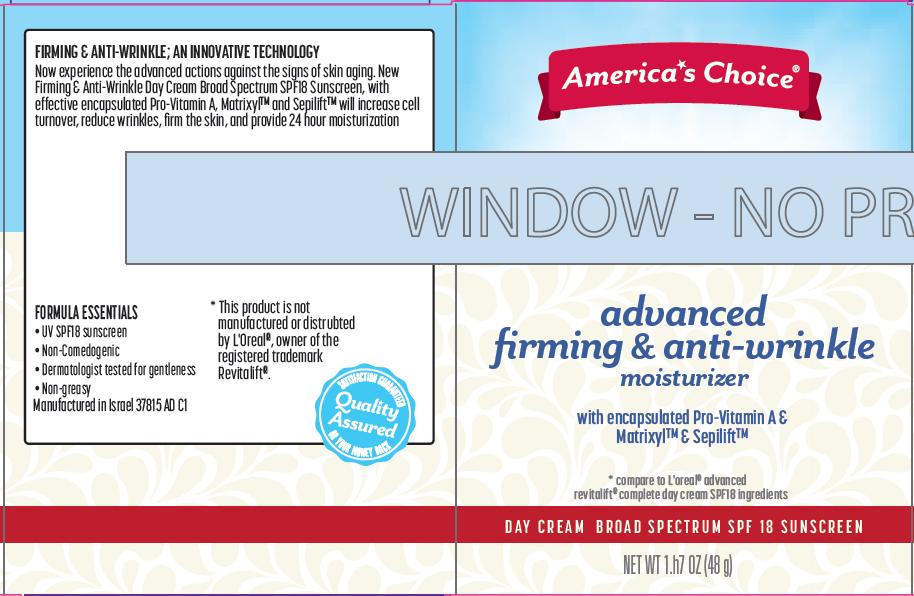 DRUG LABEL: Advanced Firming and Anti-Wrinkle Moisturizer Day Broad Spectrum SPF18 Sunscreen
NDC: 42421-815 | Form: CREAM
Manufacturer: Emilia Personal Care Inc.
Category: otc | Type: HUMAN OTC DRUG LABEL
Date: 20140110

ACTIVE INGREDIENTS: AVOBENZONE 2 g/100 g; OCTISALATE 5 g/100 g; OCTOCRYLENE 5 g/100 g
INACTIVE INGREDIENTS: WATER; CYCLOMETHICONE 6; GLYCERIN; TITANIUM DIOXIDE; GLYCERYL MONOSTEARATE; PEG-100 STEARATE; YELLOW WAX; MYRISTYL MYRISTATE; STEARIC ACID; PALMITIC ACID; DOCOSANOL; SODIUM STEAROYL LACTYLATE; .ALPHA.-TOCOPHEROL ACETATE; BUTYLENE GLYCOL; POLYSORBATE 20; PALMITOYL OLIGOPEPTIDE; PALMITOYL TETRAPEPTIDE-7; PROPYLENE GLYCOL; DIAZOLIDINYL UREA; METHYLPARABEN; PROPYLPARABEN; CETYL ALCOHOL; STEARYL ALCOHOL; DIPALMITOYL HYDROXYPROLINE; TROLAMINE; XANTHAN GUM; VITAMIN A PALMITATE; PHENOXYETHANOL; PEG-20 STEARATE; POTASSIUM SORBATE; SODIUM BENZOATE; PHENYLETHYL ALCOHOL; ALCOHOL; CHLORPHENESIN; CARBOMER COPOLYMER TYPE B (ALLYL PENTAERYTHRITOL CROSSLINKED); SOY PROTEIN

America's Choice advanced firming & anti-wrinkle moisturizer

Active ingredient

Avobenzone 2.0%
Octisalate 5.0%
Octocrylene 5.0%

Purpose

Sunscreen

Uses

- helps prevent sunburn
- If used as directed with other sun protection measures (see Directions), decreases the risk of skin cancer and early skin aging caused by the sun

Warnings

For external use only.

Do not use on

- damaged or broken skin.

When using this product

- keep out of eyes. Rinse with water to remove.

Stop use and ask a doctor

- if rash occurs.

Keep out of reach of children.

If swallowed, get medical help or contact a Poison Control Center right away.

Directions

- Apply liberally 15 minutes before sun exposure.
- Reapply at least every 2 hours
- Use water resistant sunscreen if swimming or sweating
- Children under 6 months of age: ask a doctor
- Sun Protection Measures: Spending time in the sun increases your risk of skin cancer and early skin aging. To decrease this risk, regularly use a sunscreen with a Broad Spectrum SPF value of 15 or higher and other sun protection measures including:
  - limit time in the sun, especially from 10 a.m. – 2 p.m.
  - wear long-sleeved shirts, pants, hats and sunglasses

Other Information

- protect the product in this container from excessive heat and direct sun

Inactive Ingredients

water, cyclohexasiloxane, glycerin, titanium dioxide, glyceryl stearate, PEG-100 stearate, beeswax, myristyl myristate, stearic acid, palmitic acid, polyglyceryl-10 pentastearate, behenyl alcohol, sodium steroyl lactylate, tocopheryl acetate (vitamin E), butylene glycol, carbomer, polysorbate 20, palmitoyl oligopeptide, palmitoyl tetrapeptide-7, propylene glycol, diazolidinyl urea, methylparaben, propylparaben, cetyl alcohol,stearyl alcohol, hydrolyzed soy protein, dipalmitoyl hydroxyproline, fragrance, triethanolamine, glycine soja (soybean) protein, xanthan gum, retinyl palmitate (vitamin A), phenoxyethanol, PEG-20 stearate, potassium sorbate, sodium benzoate, phenethyl alcohol, alcohol denat., chlorphenesin

Package/Label Principal Display Panel

America's Choice

advanced firming & anti-wrinkle moisturizer
with encapsulated Pro-Vitamin A & Matrixyl™ & Sepilift™

*compare to L’Oreal® advanced revitalift® complete day cream SPF18 ingredients

DAY CREAM BROAD SPECTRUM SPF 18 SUNSCREEN

NET WT 1.7 OZ (48 g)

TRIPLE-ACTION TECHNOLOGY
Advanced Anti-Wrinkle Action: Encapsulated Pro-Vitamin A and Sepilift™ will hasten skin renewal reducing the amount of fine lines and wrinkles and their depth. Results can be seen in just two weeks. The newtechnology will continually act to help fight the signs of aging.

Innovative Firming; Matrixyl™ has proven to show renewed elastin and collagen fibers*. Skin’s surface is remodeled, becoming more resilient and toned.

Continuous Moisturization & Skin Protection; Provides 24 hour moisturization to soothe dry skin. Broad spectrum UVA/UVB SPF18 protects the skin and prevents damage by UV exposure.

Directions for Use; Every day, smooth gently onto face and neck until thoroughly absorbed. Use in the AM, alone or under makeup.

Results; Skin’s elasticity is improved. Visible reduction of wrinkles and skin looks smoother, Firmer skin

Matrixyl™ is a registered trademark owned by Sederma.
Sepilift™ is a registered trademark owned by Seppic.

*In-vitro testing

FIRMING & ANTI-WRINKLE; AN INNOVATIVE TECHNOLOGY
Now experience the advanced actions against the signs of skin aging. New Firming & Anti-Wrinkle Day Cream Broad Spectrum SPF18 Sunscreen, with effective encapsulated Pro-Vitamin A, Matrixyl™ & Sepilift™ will increase cell turnover, reduce wrinkles, firm the skin, and provide 24 hour moisturization

FORMULA ESSENTIALS

- UV SPF18 sunscreen
- Non-Comedogenic
- Dermatologist tested for gentleness
- Non-greasy

Manufactured in Israel 37815 AD C1

*This product is not manufactured or distributed by L’Oreal, owner of the registered trademark Revitalift®.

Carton Label